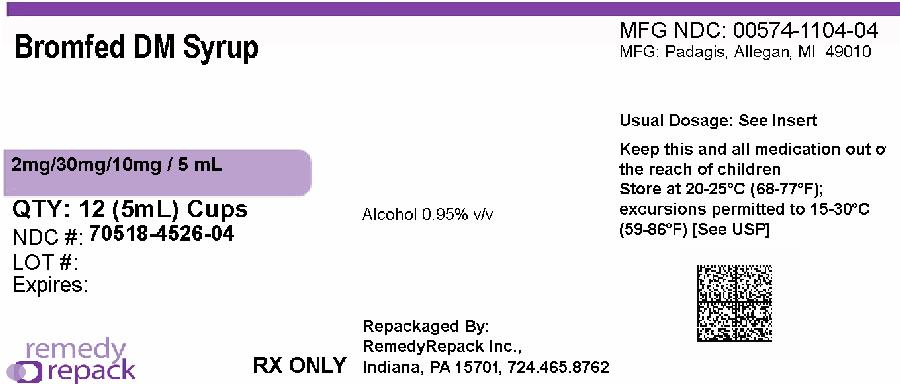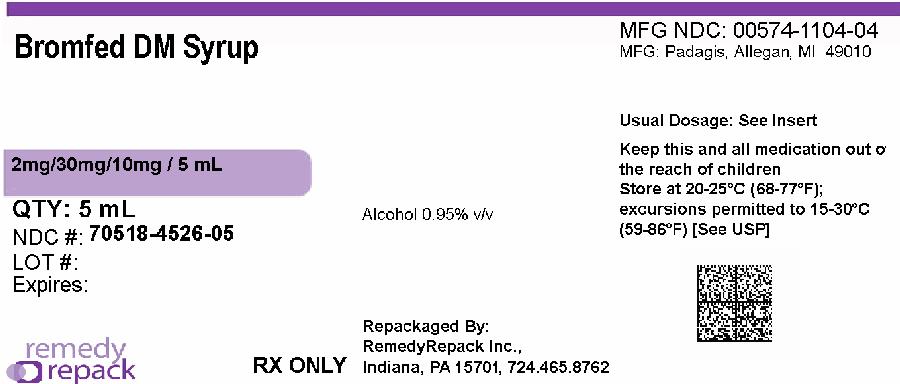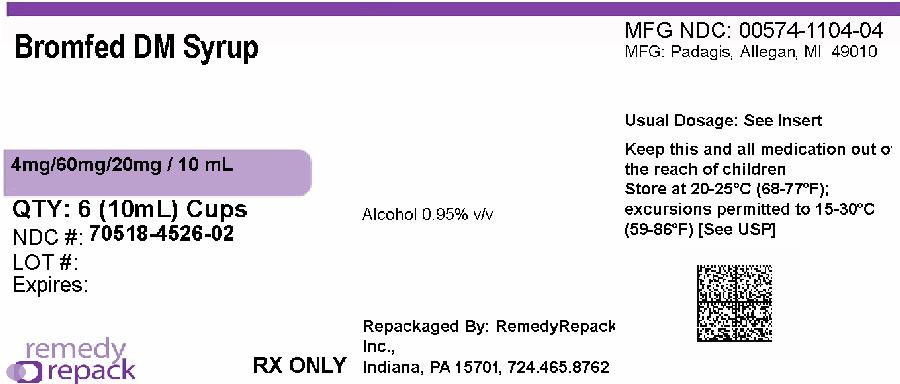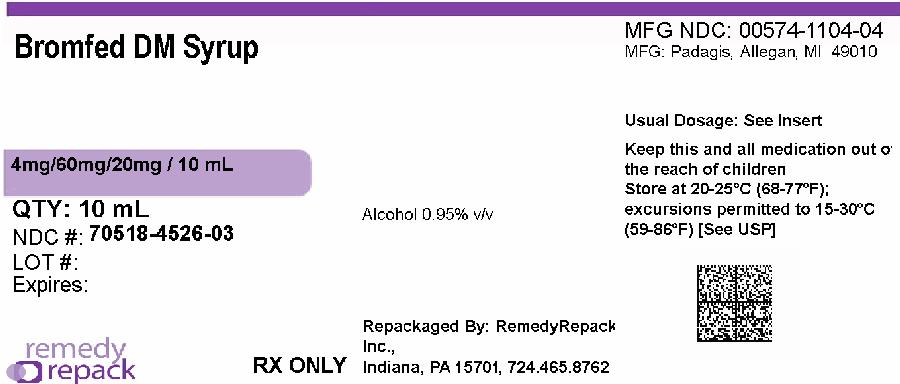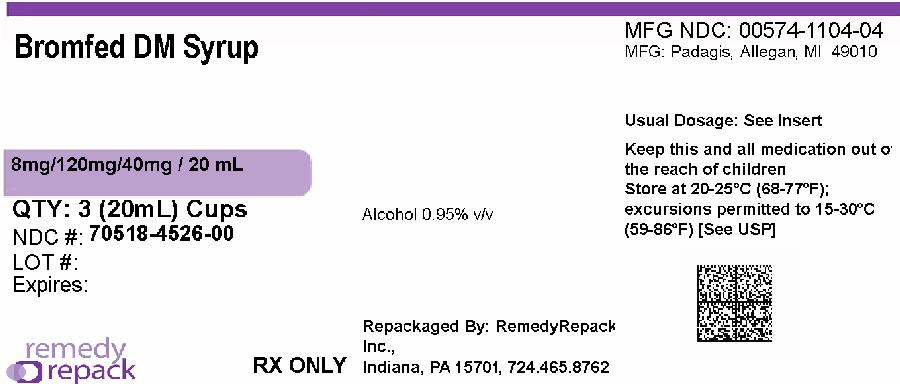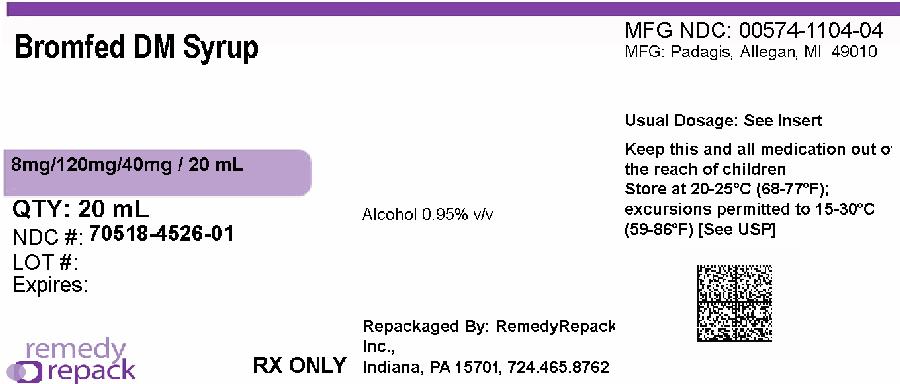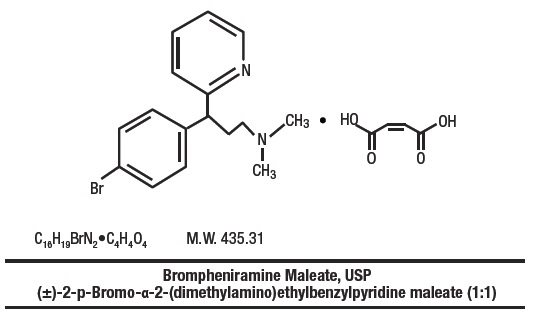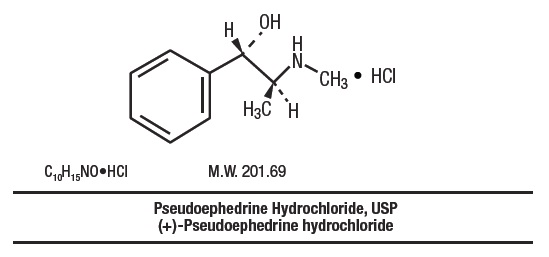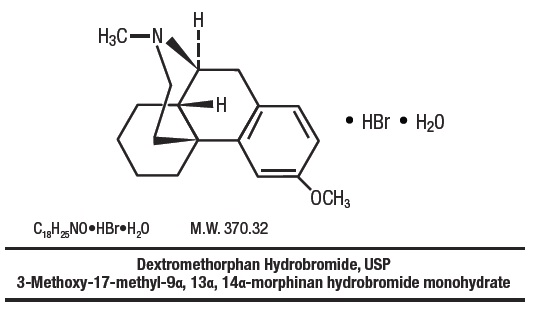 DRUG LABEL: Brompheniramine Maleate, Pseudoephedrine Hydrochloride and Dextromethorphan Hydrobromide
NDC: 70518-4526 | Form: SYRUP
Manufacturer: REMEDYREPACK INC.
Category: prescription | Type: HUMAN PRESCRIPTION DRUG LABEL
Date: 20260113

ACTIVE INGREDIENTS: BROMPHENIRAMINE MALEATE 2 mg/5 mL; PSEUDOEPHEDRINE HYDROCHLORIDE 30 mg/5 mL; DEXTROMETHORPHAN HYDROBROMIDE 10 mg/5 mL
INACTIVE INGREDIENTS: ALCOHOL; ANHYDROUS CITRIC ACID; GLYCERIN; METHYLPARABEN; PROPYLENE GLYCOL; WATER; SODIUM BENZOATE; SUCROSE; FD&C RED NO. 40; SODIUM CITRATE, UNSPECIFIED FORM

Brompheniramine Maleate, Pseudoephedrine Hydrochloride and Dextromethorphan Hydrobromide Oral Syrup

Rx only

DESCRIPTION

Brompheniramine Maleate, Pseudoephedrine Hydrochloride and Dextromethorphan Hydrobromide Oral Syrup is a clear, light pink syrup with a butterscotch flavor.

Each 5 mL (1 teaspoonful) contains:

Brompheniramine Maleate, USP ................. 2 mg

Pseudoephedrine Hydrochloride, USP ........ 30 mg

Dextromethorphan Hydrobromide, USP ...... 10 mg

Alcohol 0.95% v/v

In a palatable, aromatic vehicle.

Inactive Ingredients: alcohol, artificial butterscotch flavor, citric acid anhydrous, glycerin, methylparaben, propylene glycol, purified water, sodium benzoate, sodium citrate, sucrose, and FD&C Red No. 40. It may contain 10% citric acid solution or 10% sodium citrate solution for pH adjustment. The pH range is between 3.0 and 6.0.

Antihistamine/Nasal Decongestant/Antitussive syrup for oral administration.

CLINICAL PHARMACOLOGY

Brompheniramine maleate is a histamine antagonist, specifically an H1-receptor-blocking agent belonging to the alkylamine class of antihistamines. Antihistamines appear to compete with histamine for receptor sites on effector cells. Brompheniramine also has anticholinergic (drying) and sedative effects. Among the antihistaminic effects, it antagonizes the allergic response (vasodilation, increased vascular permeability, increased mucus secretion) of nasal tissue. Brompheniramine is well absorbed from the gastrointestinal tract, with peak plasma concentration after single, oral dose of 4 mg reached in 5 hours; urinary excretion is the major route of elimination, mostly as products of biodegradation; the liver is assumed to be the main site of metabolic transformation.

Pseudoephedrine acts on sympathetic nerve endings and also on smooth muscle, making it useful as a nasal decongestant. The nasal decongestant effect is mediated by the action of pseudoephedrine on α-sympathetic receptors, producing vasoconstriction of the dilated nasal arterioles. Following oral administration, effects are noted within 30 minutes with peak activity occurring at approximately one hour.

Dextromethorphan acts centrally to elevate the threshold for coughing. It has no analgesic or addictive properties. The onset of antitussive action occurs in 15 to 30 minutes after administration and is of long duration.

INDICATIONS AND USAGE

For relief of coughs and upper respiratory symptoms, including nasal congestion, associated with allergy or the common cold.

CONTRAINDICATIONS

Hypersensitivity to any of the ingredients. Do not use in the newborn, in premature infants, in nursing mothers, or in patients with severe hypertension or severe coronary artery disease. Do not use dextromethorphan in patients receiving monoamine oxidase (MAOI) inhibitors (see PRECAUTIONS – Drug Interactions).

Antihistamines should not be used to treat lower respiratory tract conditions including asthma.

WARNINGS

Especially in infants and small children, antihistamines in overdosage may cause hallucinations, convulsions, and death.

Antihistamines may diminish mental alertness. In the young child, they may produce excitation.

PRECAUTIONS

General

Because of its antihistamine component, Brompheniramine Maleate, Pseudoephedrine Hydrochloride and Dextromethorphan Hydrobromide Oral Syrup should be used with caution in patients with a history of bronchial asthma, narrow angle glaucoma, gastrointestinal obstruction, or urinary bladder neck obstruction. Because of its sympathomimetic component, Brompheniramine Maleate, Pseudoephedrine Hydrochloride and Dextromethorphan Hydrobromide Oral Syrup should be used with caution in patients with diabetes, hypertension, heart disease, or thyroid disease.

Information for Patients

Patients should be warned about engaging in activities requiring mental alertness, such as driving a car or operating dangerous machinery.

Repackaged By / Distributed By: RemedyRepack Inc.

625 Kolter Drive, Indiana, PA 15701

(724) 465-8762

Drug Interactions

Monoamine oxidase (MAO) inhibitors

Hyperpyrexia, hypotension, and death have been reported coincident with the coadministration of MAO inhibitors and products containing dextromethorphan. In addition, MAO inhibitors prolong and intensify the anticholinergic (drying) effects of antihistamines and may enhance the effect of pseudoephedrine. Concomitant administration of Brompheniramine Maleate, Pseudoephedrine Hydrochloride and Dextromethorphan Hydrobromide Oral Syrup and MAO inhibitors should be avoided (see CONTRAINDICATIONS).

Central Nervous System (CNS) depressants

Antihistamines have additive effects with alcohol and other CNS depressants (hypnotics, sedatives, tranquilizers, antianxiety agents, etc.).

Antihypertensive drugs

Sympathomimetic may reduce the effects of antihypertensive drugs.

Carcinogenesis, Mutagenesis, Impairment of Fertility

Animal studies of Brompheniramine Maleate, Pseudoephedrine Hydrochloride and Dextromethorphan Hydrobromide Oral Syrup to assess the carcinogenic and mutagenic potential or the effect on fertility have not been performed.

Pregnancy

Teratogenic Effects

Pregnancy Category C

Animal reproduction studies have not been conducted with Brompheniramine Maleate, Pseudoephedrine Hydrochloride and Dextromethorphan Hydrobromide Oral Syrup. It is also not known whether Brompheniramine Maleate, Pseudoephedrine Hydrochloride and Dextromethorphan Hydrobromide Oral Syrup can cause fetal harm when administered to a pregnant woman or can affect reproduction capacity. It should be given to a pregnant woman only if clearly needed.

Reproduction studies of brompheniramine maleate (a component of Brompheniramine Maleate, Pseudoephedrine Hydrochloride and Dextromethorphan Hydrobromide Oral Syrup) in rats and mice at doses up to 16 times the maximum human doses have revealed no evidence of impaired fertility or harm to the fetus.

Nursing Mothers

Because of the higher risk of intolerance of antihistamines in small infants generally, and in newborns and prematures in particular, Brompheniramine Maleate, Pseudoephedrine Hydrochloride and Dextromethorphan Hydrobromide Oral Syrup is contraindicated in nursing mothers.

Pediatric Use

Safety and effectiveness in pediatric patients below the age of 6 months have not been established (see DOSAGE AND ADMINISTRATION).

Geriatric Use

Clinical studies of Brompheniramine Maleate, Pseudoephedrine Hydrochloride and Dextromethorphan Hydrobromide Oral Syrup did not include sufficient numbers of subjects aged 65 and over to determine whether they respond differently from younger subjects. However, antihistamines are more likely to cause dizziness, sedation, and hypotension in elderly patients. The elderly are also more likely to experience adverse reactions to sympathomimetics.

In general, dose selection for an elderly patient should be cautious, usually starting at the low end of the dosing range, reflecting the greater frequency of decreased hepatic, renal, or cardiac function, and of concomitant disease or other drug therapy.

ADVERSE REACTIONS

The most frequent adverse reactions to Brompheniramine Maleate, Pseudoephedrine Hydrochloride and Dextromethorphan Hydrobromide Oral Syrup are: sedation; dryness of mouth, nose and throat; thickening of bronchial secretions; dizziness.

Other adverse reactions may include:

Dermatologic:Urticaria, drug rash, photosensitivity, pruritus.

Cardiovascular System:Hypotension, hypertension, cardiac arrhythmias, palpitation.

CNS:Disturbed coordination, tremor, irritability, insomnia, visual disturbances, weakness, nervousness, convulsions, headache, euphoria, and dysphoria.

G.U. System:Urinary frequency, difficult urination.

G.I. System:Epigastric discomfort, anorexia, nausea, vomiting, diarrhea, constipation.

Respiratory System:Tightness of chest and wheezing, shortness of breath.

Hematologic System:Hemolytic anemia, thrombocytopenia, agranulocytosis.

OVERDOSAGE

Signs and Symptoms

Central nervous system effects from overdosage of brompheniramine may vary from depression to stimulation, especially in children. Anticholinergic effects may be noted. Toxic doses of pseudoephedrine may result in CNS stimulation, tachycardia, hypertension, and cardiac arrhythmias; signs of CNS depression may occasionally be seen. Dextromethorphan in toxic doses will cause drowsiness, ataxia, nystagmus, opisthotonos, and convulsive seizures.

Toxic Doses

Data suggest that individuals may respond in an unexpected manner to apparently small amounts of a particular drug. A 2½-year-old child survived the ingestion of 21 mg/kg of dextromethorphan exhibiting only ataxia, drowsiness, and fever, but seizures have been reported in 2 children following the ingestion of 13-17 mg/kg. Another 2½-year-old child survived a dose of 300-900 mg of brompheniramine. The toxic dose of pseudoephedrine should be less than that of ephedrine, which is estimated to be 50 mg/kg.

Treatment

Induce emesis if patient is alert and is seen prior to 6 hours following ingestion. Precautions against aspiration must be taken, especially in infants and small children. Gastric lavage may be carried out, although in some instances tracheostomy may be necessary prior to lavage. Naloxone hydrochloride 0.005 mg/kg intravenously may be of value in reversing the CNS depression that may occur from an overdose of dextromethorphan. CNS stimulants may counter CNS depression. Should CNS hyperactivity or convulsive seizures occur, intravenous short-acting barbiturates may be indicated. Hypertensive responses and/or tachycardia should be treated appropriately. Oxygen, intravenous fluids, and other supportive measures should be employed as indicated.

DOSAGE AND ADMINISTRATION

Adults and pediatric patients 12 years of age and over: 10 mL (2 teaspoonfuls) every 4 hours. Children 6 to under 12 years of age: 5 mL (1 teaspoonful) every 4 hours. Children 2 to under 6 years of age: 2.5 mL (½ teaspoonful) every 4 hours. Infants 6 months to under 2 years of age: Dosage to be established by a physician.

Do not exceed 6 doses during a 24-hour period.

HOW SUPPLIED

Brompheniramine Maleate, Pseudoephedrine Hydrochloride and Dextromethorphan Hydrobromide Oral Syrup is a clear, light pink-colored, butterscotch-flavored syrup containing in each 5 mL (1 teaspoonful) brompheniramine maleate 2 mg, pseudoephedrine hydrochloride 30 mg and dextromethorphan hydrobromide 10 mg, available in the following sizes:

8mg/120mg/40mg / 20mL

NDC: 70518-4526-00

NDC: 70518-4526-01

NDC: 70518-4526-02

NDC: 70518-4526-03

NDC: 70518-4526-04

NDC: 70518-4526-05

PACKAGING: 3 in 1 BOX

PACKAGING: 20 mL in 1 CUP

PACKAGING: 6 in 1 BOX

PACKAGING: 10 mL in 1 CUP

PACKAGING: 12 in 1 BOX

PACKAGING: 5 mL in 1 CUP

Store at 20° to 25°C (68° to 77°F) [see USP Controlled Room Temperature].

Keep Tightly Closed

Dispense in a tight, light-resistant container as defined in the USP.

Rx Only

Repackaged and Distributed By:

Remedy Repack, Inc.

625 Kolter Dr. Suite #4 Indiana, PA 1-724-465-8762

RECOMMENDED STORAGE

Store at 20° to 25°C (68° to 77°F) [see USP Controlled Room Temperature].

Keep Tightly Closed

Dispense in a tight, light-resistant container as defined in the USP.

Rx Only

Repackaged and Distributed By:

Remedy Repack, Inc.

625 Kolter Dr. Suite #4 Indiana, PA 1-724-465-8762

PACKAGE LABEL

DRUG: Brompheniramine Maleate, Pseudoephedrine Hydrochloride and Dextromethorphan Hydrobromide

GENERIC: Brompheniramine Maleate, Pseudoephedrine Hydrochloride and Dextromethorphan Hydrobromide

DOSAGE: SYRUP

ADMINSTRATION: ORAL

NDC: 70518-4526-0

NDC: 70518-4526-1

NDC: 70518-4526-2

NDC: 70518-4526-3

NDC: 70518-4526-4

NDC: 70518-4526-5

COLOR: pink

FLAVOR: BUTTERSCOTCH

OUTER PACKAGING: 3 in 1 BOX

PACKAGING: 20 mL in 1 CUP
OUTER PACKAGING: 6 in 1 BOX
PACKAGING: 10 mL in 1 CUP

OUTER PACKAGING: 12 in 1 BOX

PACKAGING: 5 mL in 1 CUP

ACTIVE INGREDIENT(S):

- PSEUDOEPHEDRINE HYDROCHLORIDE 30mg in 5mL
- DEXTROMETHORPHAN HYDROBROMIDE 10mg in 5mL
- BROMPHENIRAMINE MALEATE 2mg in 5mL

INACTIVE INGREDIENT(S):

- ALCOHOL
- ANHYDROUS CITRIC ACID
- GLYCERIN
- METHYLPARABEN
- PROPYLENE GLYCOL
- WATER
- SODIUM BENZOATE
- SUCROSE
- FD&C RED NO. 40
- SODIUM CITRATE, UNSPECIFIED FORM